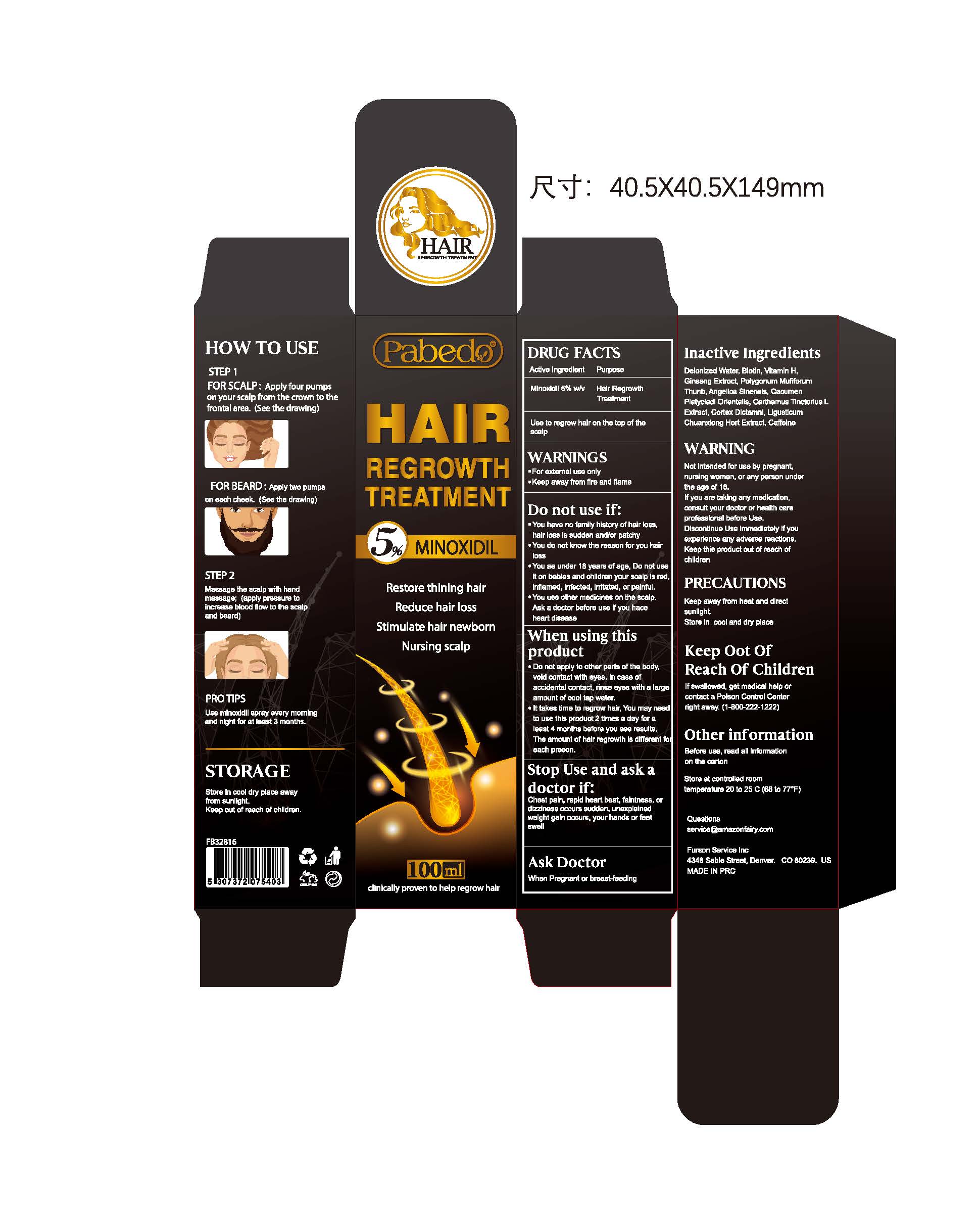 DRUG LABEL: Pabedo 5% Minoxidil Hair Growth serum
NDC: 84026-101 | Form: SOLUTION
Manufacturer: Shenzhen Nuoshengjia Technology Co., Ltd.
Category: otc | Type: HUMAN OTC DRUG LABEL
Date: 20240118

ACTIVE INGREDIENTS: MINOXIDIL 0.05 g/1 mL
INACTIVE INGREDIENTS: WATER; LIGUSTICUM SINENSE SUBSP. CHUANXIONG ROOT; POLYGONATUM MULTIFLORUM ROOT; ANGELICA SINENSIS ROOT OIL; ASIAN GINSENG; PLATYCLADUS ORIENTALIS LEAF; CAFFEINE; BIOTIN; SAFFLOWER; CORDIA DICHOTOMA WHOLE

Pabedo 5% Minoxidil Hair Growth serum

ACTIVE INGREDIENT

Minoxidil 5%

PURPOSE

Hair Regrowth Treatment

WHEN USING

to regrow hair on the top of the scalp

WARNINGS

For external use only

Keep away from fire and flame

Avoid contact with eyes

DO NOT USE

You have no family history of hair loss,hair loss is sudden and/or patchy

you are under 18 years of age.Do not use it on babies and children

WHEN USING

Do not apply on other parts of the body

void contact with eyes. In case of accidental contact, rinse eyes with a large amount of cool tap water

It takes time to regrow hair. You may need to use this product 2 times a day for a least 4 months before you see results, The amount of hair regrowth is different for each person

STOP USE

chest pain, rapid heart beat, faintness, or dizziness occurs

sudden, unexplained weight gain occurs

your hands or feet swell

scalp irritation or redness occurs

ASK DOCTOR

When Pregnant or breast-feeding

KEEP OUT OF REACH OF CHILDREN

When Pregnant or breast-feeding

DOSAGE AND ADMINISTRATION

1. Apply 1 ML(few drops) directly onto scalp on the hairloss area.
2. Use fingertips to massage solution into skinjhair for2-3 minutes.
3. Allow time for hair tofully absorb Growth Oil For bestresults, use twice daily on clean dry hair

STORAGE AND HANDLING

Before use, read all information on the carton

Store at controlled room temperature 20 to 25 C (68 to 77°F)

INACTIVE INGREDIENT

Biotin
Vitamin H
Water
Ginseng Extroct
polygonum multiflorum Thunb
Angelica Sinensis
Cacumen Platycladi Orientalis
Carthamus Tinctorius L Extract
Ligusticum Chuanxiong Hort Extract
Cortex Dictamni
caffeine

INDICATIONS AND USAGE

to regrow hair on the top of the scalp
Apply 1 ML(few drops) directly onto scalp on the hairloss area.
Use fingertips to massage solution into skinjhair for2-3 minutes.
Allow time for hair tofully absorb Growth Oil For bestresults, use twice daily on clean dry hair